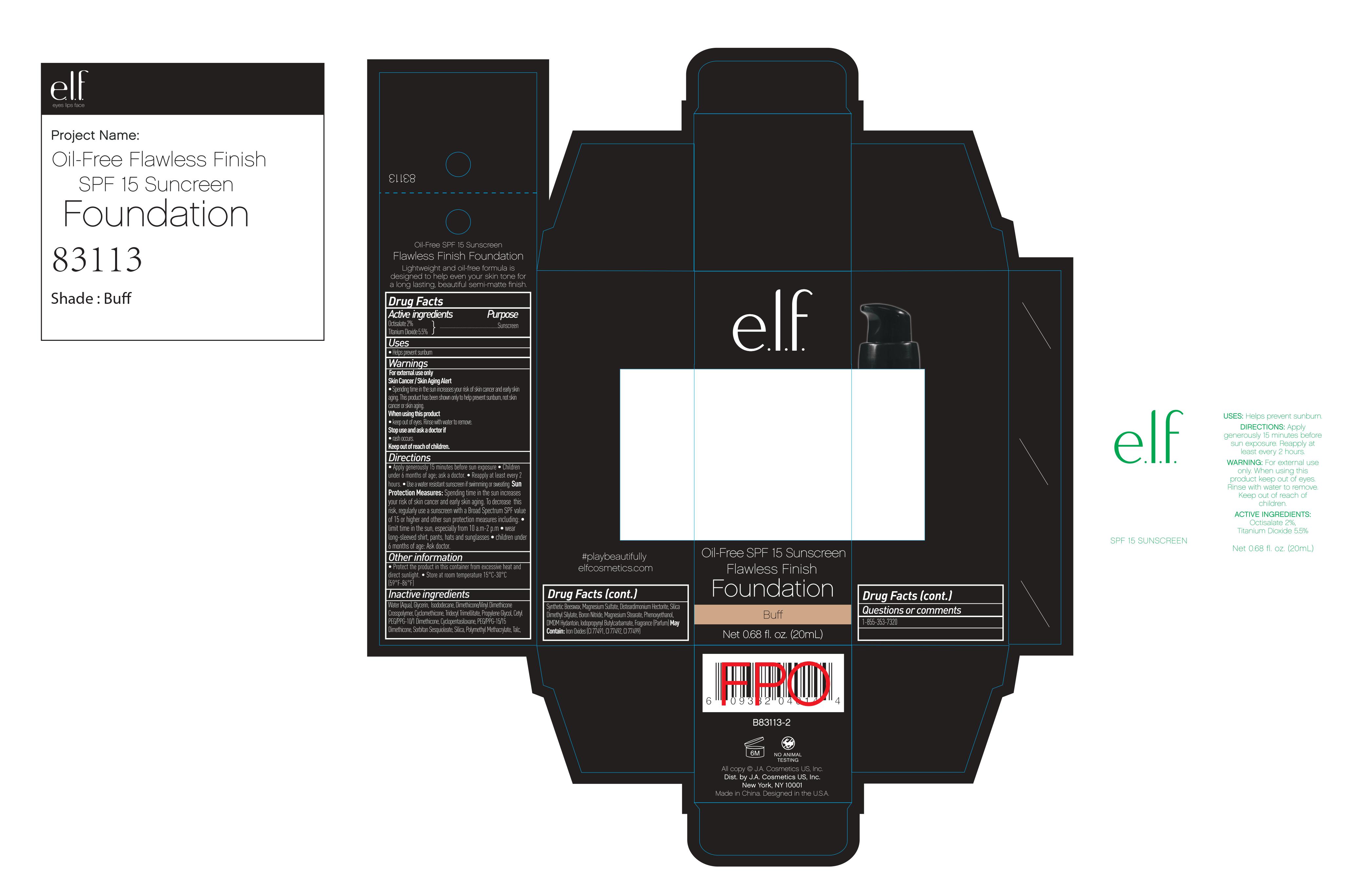 DRUG LABEL: ELF Oil free flawless Finish SPF 15 Sunscreen Foundation Buff
NDC: 76354-627 | Form: CREAM
Manufacturer: e.l.f. Cosmetics, Inc
Category: otc | Type: HUMAN OTC DRUG LABEL
Date: 20241212

ACTIVE INGREDIENTS: OCTISALATE 2 g/100 mL; TITANIUM DIOXIDE 5.5 g/100 mL
INACTIVE INGREDIENTS: WATER; ISODODECANE; CETYL PEG/PPG-10/1 DIMETHICONE (HLB 2); GLYCERIN; DIMETHICONE/VINYL DIMETHICONE CROSSPOLYMER (SOFT PARTICLE); CYCLOMETHICONE; FERRIC OXIDE RED; FERRIC OXIDE YELLOW; FERROSOFERRIC OXIDE; PROPYLENE GLYCOL; SORBITAN SESQUIOLEATE; BORON NITRIDE; MAGNESIUM SULFATE, UNSPECIFIED FORM; MAGNESIUM STEARATE; BENTONITE; PHENOXYETHANOL; SILICA DIMETHYL SILYLATE; MINERAL OIL; TALC; IODOPROPYNYL BUTYLCARBAMATE; DMDM HYDANTOIN

Drug Fact

Active Ingredient:

Octisalate: 2.0%

Titanium Dioxide: 5.5%

Purpose:

Sunscreen

Uses:

Help prevent sunburn

Warning:

For external use only

Skin Cancer/ Skin Aging Alert: Spending time in the sun increases your risk of skin cancer or early skin aging. This product has been shown to only protect you from sunburn, not skin cancer or sking aging.

When using this product:

Keep out of eyes. Rinse with water to remove.

Stop Use and Ask a Doctor if:

Rash occurs

Keep Out of Reach of Children

Directions:

For sunscreen use:

Apply generously 15 min before sun exposure.

Children under six months of age: ask a doctor.

Reapply at least every two hours.

Use a water resistant sunscreen if swimming or sweating

Sun Protection Measures:

Spending time in sun increases your risk of skin cancer or early skin aging. To decrease the risk, regularly use a sunscreen with broad spectrum SPF value of 15 or higher and other sun protection measures including

Other Information:

Protect this product in the container from excessive heat and direct sun

Store at room temperature 15-30 C (59-86F)

- Limit time in the sun, especially from 10 am to 2 pm
- Wear long sleeved shirts, pants, hats, and sunglasses.
- Children under six months of age: ask a doctor

Inactive Ingredient:

Water, Dimethicone, Glycerin, Isododecane, Dimethicone/VinylDimethicone Crosspolymer, Cyclomethicone, Propylene Glycol, CETYL PEG/PPG-10/1 DIMETHICONE, Cyclopentasiloxane, Sorbitan Sesquioleate, Silica, Polymethyl Methacrylate, Talc, Synthetic Beewax, Magnesium Sulfate, Silica Dimethyl Silylate, Boron Nitride, Magnesium Stearate, Phenoxyethanol, DMDM Hydantoin, Iodopropynyl Butylcarbamate, Bentonite, Fragrance

May contain:

Iron Oxides (CI 77491, CI 77492, CI 77499)